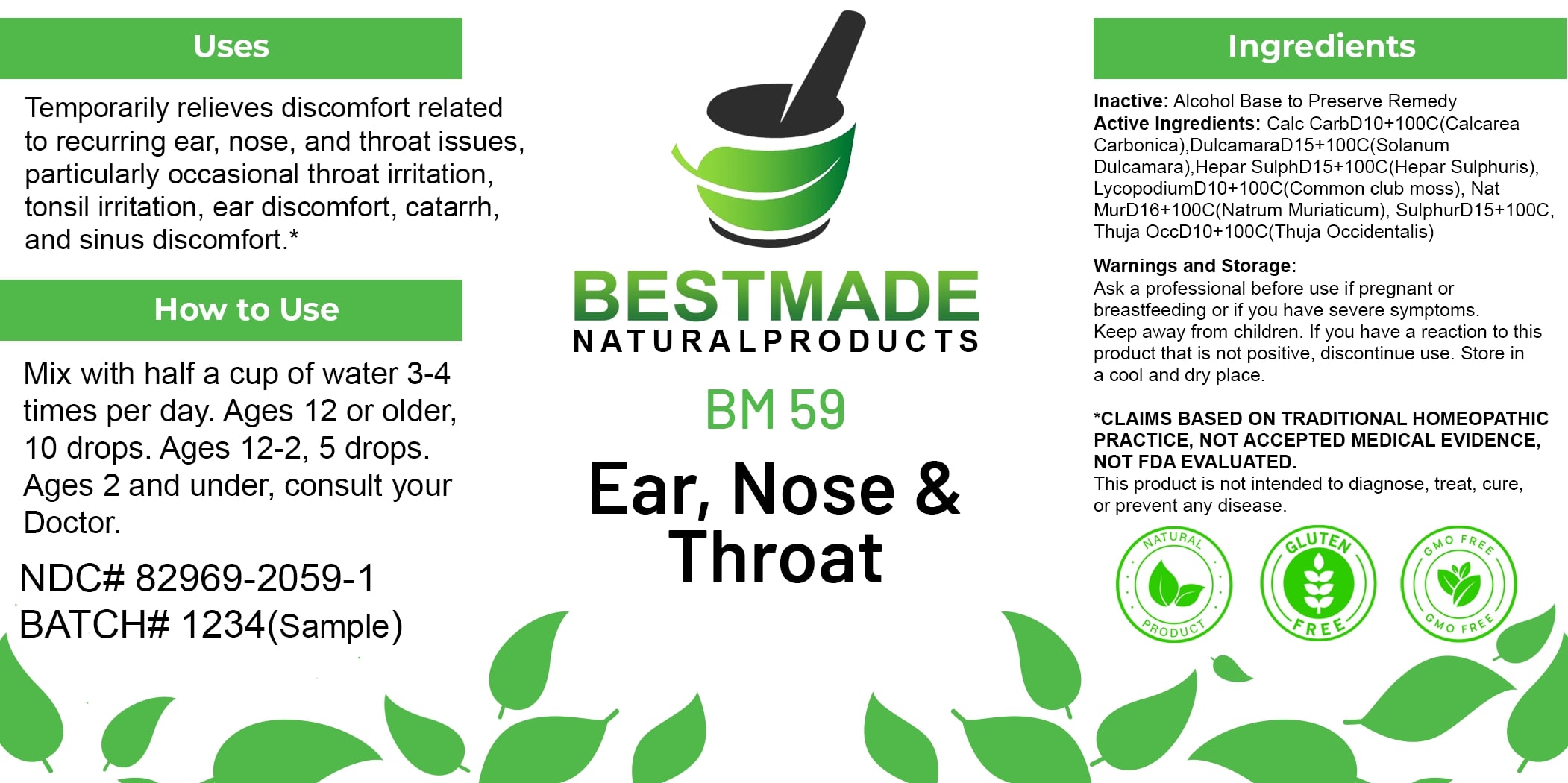 DRUG LABEL: Bestmade Natural Products BM59
NDC: 82969-2059 | Form: LIQUID
Manufacturer: Bestmade Natural Products
Category: homeopathic | Type: HUMAN OTC DRUG LABEL
Date: 20250124

ACTIVE INGREDIENTS: OYSTER SHELL CALCIUM CARBONATE, CRUDE 100 [hp_C]/100 [hp_C]; SOLANUM DULCAMARA TOP 100 [hp_C]/100 [hp_C]; CALCIUM SULFIDE 100 [hp_C]/100 [hp_C]; LYCOPODIUM CLAVATUM SPORE 100 [hp_C]/100 [hp_C]; SULFUR 100 [hp_C]/100 [hp_C]; SODIUM CHLORIDE 100 [hp_C]/100 [hp_C]; THUJA OCCIDENTALIS LEAFY TWIG 100 [hp_C]/100 [hp_C]
INACTIVE INGREDIENTS: ALCOHOL 100 [hp_C]/100 [hp_C]

BM59

DOSAGE AND ADMINISTRATION

How to Use

Mix with half a cup of water 3-4 times per day. Ages 12 or older, 10 drops. Ages 12-2, 5 drops. Ages 2 and under, consult your Doctor.

INACTIVE INGREDIENT

Ingredients

Inactive: Alcohol Base to Preserve Remedy

ACTIVE INGREDIENT

Active Ingredients: Calc Carb D10+100C (Calcarea Carbonica), Dulcamara D15+100C (Solanum Dulcamara), Hepar Sulph D15+100C (Hepar Sulphuris), Lycopodium D10+100C (Common club moss), Nat Mur D16+100C (Natrum Muriaticum), Sulphur D15+100C, Thuja Occ D10+100C (Thuja Occidentalis)

Uses

Temporarily relieves discomfort related to recurring ear, nose, and throat issues, particularly occasional throat irritation, tonsil irritation, ear discomfort, catarrh, and sinus discomfort.*

*CLAIMS BASED ON TRADITIONAL HOMEOPATHIC PRACTICE, NOT ACCEPTED MEDICAL EVIDENCE. NOT FDA EVALUATED.

This product is not intended to diagnose, treat, cure, or prevent any disease.

Uses

Temporarily relieves discomfort related to recurring ear, nose, and throat issues, particularly occasional throat irritation, tonsil irritation, ear discomfort, catarrh, and sinus discomfort.*

*CLAIMS BASED ON TRADITIONAL HOMEOPATHIC PRACTICE, NOT ACCEPTED MEDICAL EVIDENCE. NOT FDA EVALUATED.

This product is not intended to diagnose, treat, cure, or prevent any disease.

KEEP OUT OF REACH OF CHILDREN

Warnings and Storage:

Ask a professional before use if pregnant or breastfeeding or if you have severe symptoms. Keep away from children. If you have a reaction to this product that is not positive, discontinue use. Store in a cool and dry place.

Warnings and Storage:

Ask a professional before use if pregnant or breastfeeding or if you have severe symptoms. Keep away from children. If you have a reaction to this product that is not positive, discontinue use. Store in a cool and dry place.

*CLAIMS BASED ON TRADITIONAL HOMEOPATHIC PRACTICE, NOT ACCEPTED MEDICAL EVIDENCE. NOT FDA EVALUATED.

This product is not intended to diagnose, treat, cure, or prevent any disease.

Entire package label